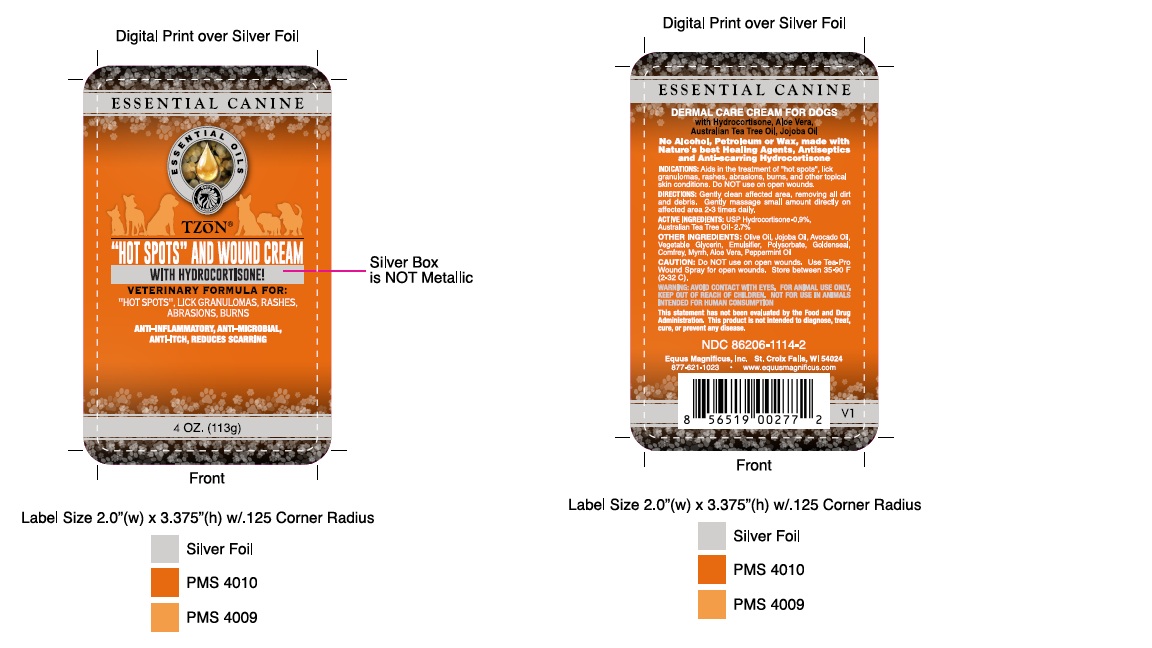 DRUG LABEL: TZoN Hot Spots and Wound Cream
NDC: 86206-1114 | Form: CREAM
Manufacturer: Equus Magnificus, Inc DBA Essential Equine & Pet
Category: animal | Type: OTC ANIMAL DRUG LABEL
Date: 20251208

ACTIVE INGREDIENTS: HYDROCORTISONE 1.02 g/113.4 g; TEA TREE OIL 3.07 g/113.4 g
INACTIVE INGREDIENTS: HYDROXYETHYL CELLULOSE, UNSPECIFIED 2.64 g/113.4 g; WATER 90.13 g/113.4 g; GLYCERIN 4.99 g/113.4 g; MYRRH OIL 0.31 g/113.4 g; GOLDENSEAL 0.31 g/113.4 g; COMFREY 0.31 g/113.4 g; CALENDULA OFFICINALIS FLOWER 0.31 g/113.4 g; AVOCADO OIL 0.91 g/113.4 g; OLIVE OIL 1.80 g/113.4 g; JOJOBA OIL 0.91 g/113.4 g; POLYSORBATE 20 4.09 g/113.4 g; PEPPERMINT OIL 0.06 g/113.4 g; sodium benzoate 0.57 g/113.4 g; ALOE VERA WHOLE 0.06 g/113.4 g; GRAPEFRUIT OIL 1.93 g/113.4 g

T-ZoN "Hot Spots" and Wound Cream

T-ZoN Hot Spots Label

TZoN Hot Spots and Wound Cream

TZoN Label

Avoid contact with eyes. For animal use only. Keep out of reach of children. Not for use in animals intended for human consumption. Do Not use on open wounds.